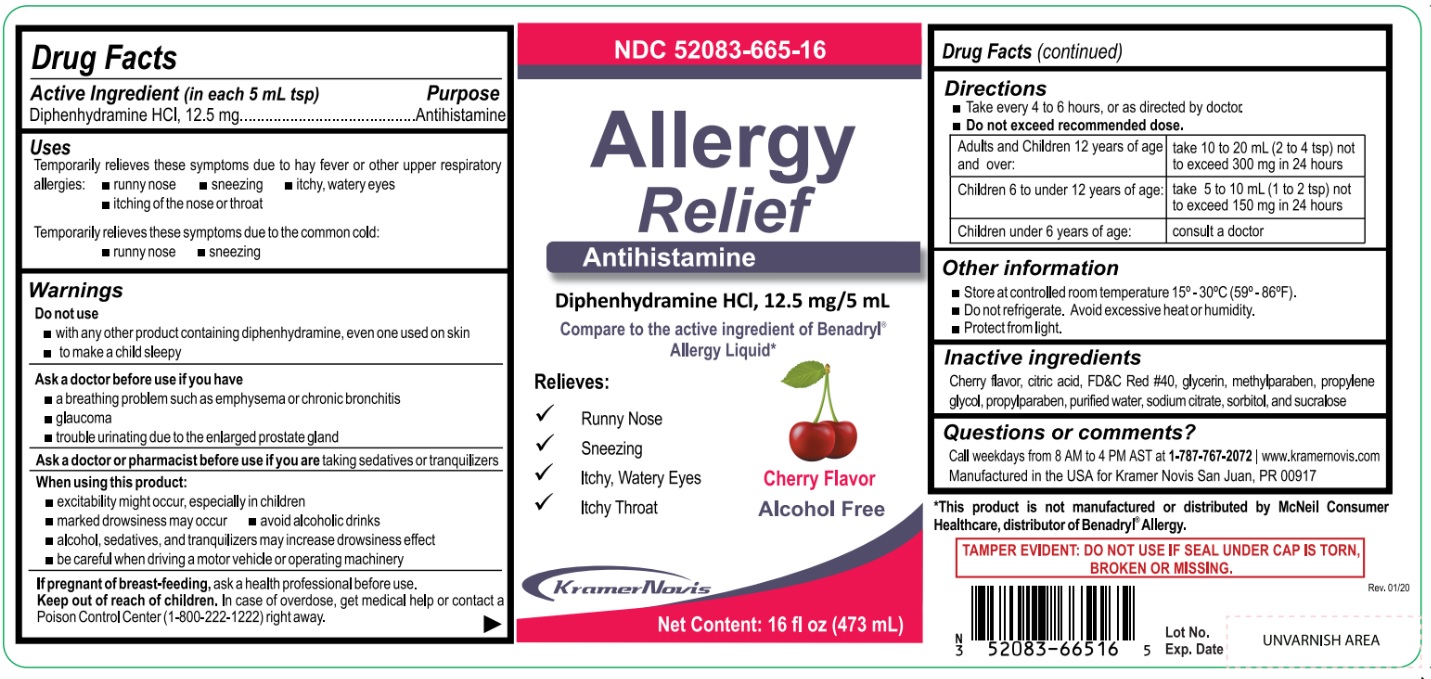 DRUG LABEL: Allergy Relief
NDC: 52083-665 | Form: LIQUID
Manufacturer: KRAMER NOVIS
Category: otc | Type: HUMAN OTC DRUG LABEL
Date: 20200303

ACTIVE INGREDIENTS: DIPHENHYDRAMINE HYDROCHLORIDE 12.5 mg/5 mL
INACTIVE INGREDIENTS: CITRIC ACID MONOHYDRATE; FD&C RED NO. 40; GLYCERIN; METHYLPARABEN; PROPYLENE GLYCOL; PROPYLPARABEN; WATER; SODIUM CITRATE, UNSPECIFIED FORM; SORBITOL; SUCRALOSE

Allergy Relief

Active Ingredient (in each 5 mL tsp)

Diphenhydramine HCL, 12.5 mg

Purpose

Antihistamine

Uses

Temporarily relieves these symptoms due to hay fever or other upper respiratory allergies:
• runny nose • sneezing • itchy, watery eyes • itching of the nose or throat

Temporarily relieves these symptoms due to the common cold:
• runny nose • sneezing

Warnings

Do not use

• with any other product containing diphenhydramine, even one used on skin

• to make a child sleepy

Ask a doctor before use if you have

• a breathing problem such as emphysema or chronic bronchitis

• glaucoma

• trouble urinating due to the enlarged prostate gland
Ask a doctor or pharmacist before use if you are taking sedatives or tranquilizers.

When using this product:

• excitability might occur, especially in children

• marked drowsiness may occur • avoid alcoholic drinks

• alcohol, sedatives, and tranquilizers may increase drowsiness effect

• be careful when driving a motor vehicle or operating machinery

If pregnant or breast-feeding, ask a health professional before use.

Keep out of reach of children. In case of overdose, get medical help or contact a Poison Control Center (1-800-222-1222) right away.

Directions

• Take every 4 to 6 hours, or as directed by doctor.
• Do not exceed recommended dose.

Adults and Children 12 years of age and over: | take 10 to 20 mL (2 to 4 tsp) not to exceed 300 mg in 24 hours
Children 6 to under 12 years of age: | take 5 to 10 mL (1 to 2 tsp) not to exceed 150 mg in 24 hours
Children under 6 years of age: | consult a doctor

Other information

• Store at controlled room temperature 15°-30°C (59°-86°F).

• Do not refrigerate. Avoid excessive heat or humidity.

• Protect from light.

Inactive ingredients

Cherry flavor, citric acid, FD&C Red #40, glycerin, methylparaben, propylene glycol, propylparaben, purified water, sodium citrate, sorbitol, and sucralose

Questions or comments?

Call weekdays from 8 AM to 4 PM AST at 1-787-767-2072 | www.kramernovis.com

Manufactured in the USA for Kramer Novis, San Juan, PR 00917

Compare to the active ingredient of Benadryl® Allergy Liquid*

Relieves:

√ Runny Nose

√ Sneezing

√ Itchy, Watery Eyes

√ Itchy Throat

Cherry Flavor

Alcohol Free

*This product is not manufactured or distributed by McNeil Consumer Healthcare, distributor of Benadryl® Allergy.

TAMPER EVIDENT: DO NOT USE IF SEAL UNDER CAP IS TORN, BROKEN OR MISSING.